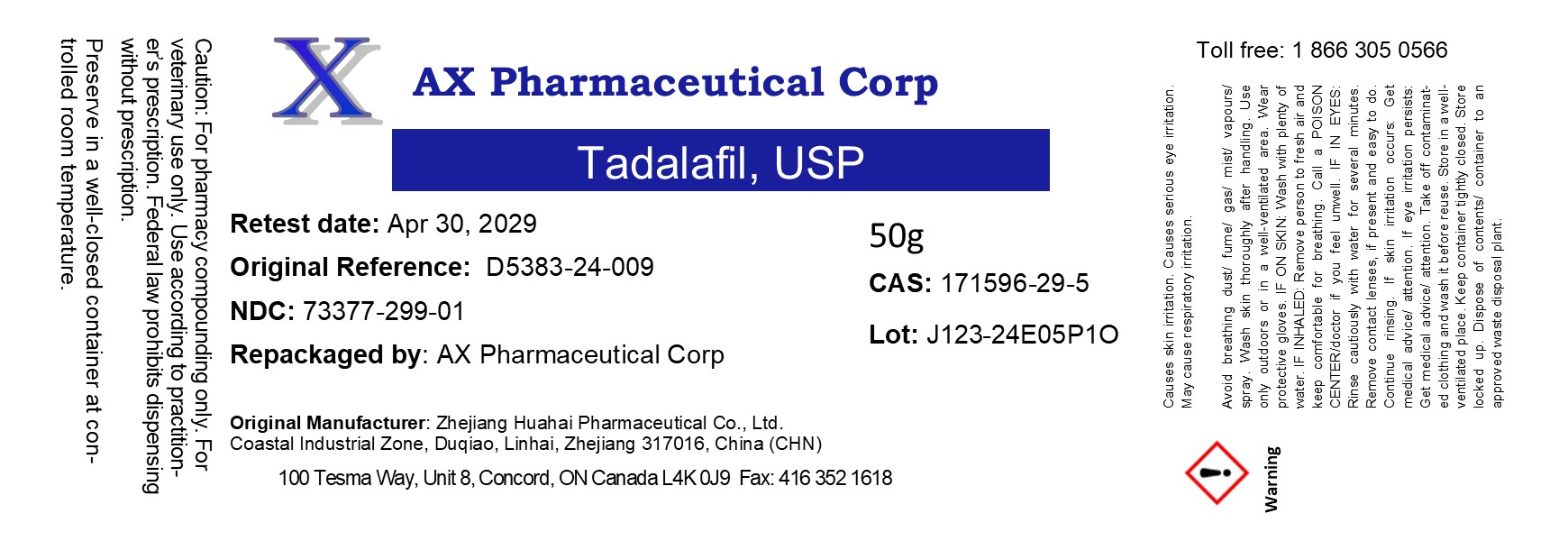 DRUG LABEL: Tadalafil
NDC: 73377-299 | Form: POWDER
Manufacturer: AX Pharmaceutical Corp
Category: other | Type: BULK INGREDIENT - ANIMAL DRUG
Date: 20241030

ACTIVE INGREDIENTS: Tadalafil 1 g/1 g

Tadalafil